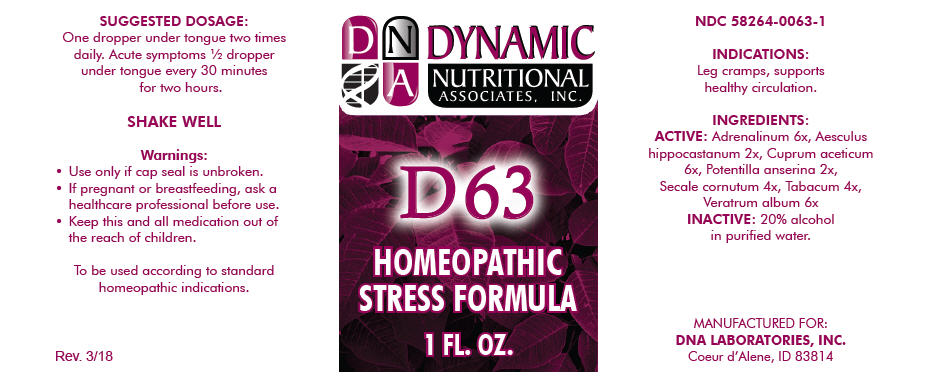 DRUG LABEL: D-63
NDC: 58264-0063 | Form: SOLUTION
Manufacturer: DNA Labs, Inc.
Category: homeopathic | Type: HUMAN OTC DRUG LABEL
Date: 20250113

ACTIVE INGREDIENTS: EPINEPHRINE 6 [hp_X]/1 mL; HORSE CHESTNUT 2 [hp_X]/1 mL; CUPRIC ACETATE 6 [hp_X]/1 mL; POTENTILLA ANSERINA WHOLE 2 [hp_X]/1 mL; CLAVICEPS PURPUREA SCLEROTIUM 4 [hp_X]/1 mL; TOBACCO LEAF 4 [hp_X]/1 mL; VERATRUM ALBUM ROOT 6 [hp_X]/1 mL
INACTIVE INGREDIENTS: ALCOHOL; WATER

D-63

NDC 58264-0063-1

INDICATIONS

PURPOSE

Leg cramps, supports healthy circulation.

INGREDIENTS

ACTIVE

Adrenalinum 6x, Aesculus hippocastanum 2x, Cuprum aceticum 6x, Potentilla anserina 2x, Secale cornutum 4x, Tabacum 4x, Veratrum album 6x

INACTIVE

20% alcohol in purified water.

SUGGESTED DOSAGE

One dropper under tongue two times daily. Acute symptoms ½ dropper under tongue every 30 minutes for two hours.

STORAGE AND HANDLING

SHAKE WELL

Warnings

- Use only if cap seal is unbroken.

PREGNANCY OR BREAST FEEDING

- If pregnant or breastfeeding, ask a healthcare professional before use.

KEEP OUT OF REACH OF CHILDREN

- Keep this and all medication out of the reach of children.

To be used according to standard homeopathic indications.

PRINCIPAL DISPLAY PANEL - 1 FL. OZ. Bottle Label

DYNAMIC
NUTRITIONAL
ASSOCIATES, INC.

D 63

HOMEOPATHIC
STRESS FORMULA

1 FL. OZ.